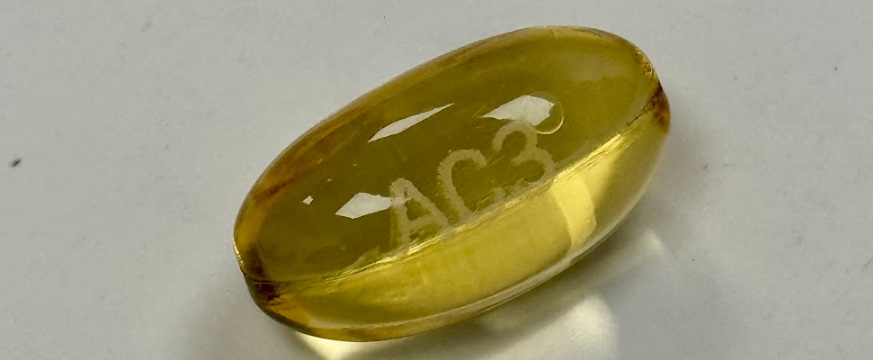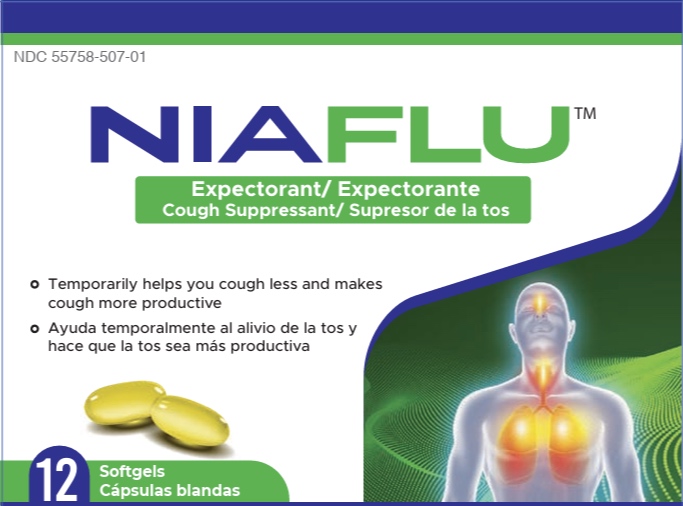 DRUG LABEL: Niaflu
NDC: 55758-507 | Form: CAPSULE, LIQUID FILLED
Manufacturer: Pharmadel LLC
Category: otc | Type: HUMAN OTC DRUG LABEL
Date: 20251217

ACTIVE INGREDIENTS: DEXTROMETHORPHAN HYDROBROMIDE 20 mg/1 1; GUAIFENESIN 400 mg/1 1
INACTIVE INGREDIENTS: GLYCERIN; POLYETHYLENE GLYCOL 400; GELATIN; POVIDONE K30; PROPYLENE GLYCOL; WATER; SORBITOL; TITANIUM DIOXIDE; 1,4-SORBITAN; SODIUM HYDROXIDE

Niaflu (HHH)

Active Ingredients and Purposes

.

PURPOSE

Active ingredients (in each softgel) | Purposes
Dextromethorphan HBr 20 mg ...... | Cough suppressant
Guaifenesin 400 mg ..... | Expectorant

Uses

Temporarily alleviates common cold/flu symptoms:

- cough due to minor throat and bronchial irritation
- helps loosen phlegm (mucus) and thin bronchial secretions to
- drain bronchial tubes
- make coughs more productive

Warnings

Do not use

- if you are now taking a prescription monoamine oxidase inhibitor (MAOI) (certain drugs for depression, psychiatric or emotional conditions, or Parkinson's disease), or for 2 weeks after stopping the MAOI drug. If you do not know if your prescription drug contains an MAOI, ask a doctor or pharmacist before taking this product.

Ask a doctor before use if you have

- a cough that is accompanied by excessive phlegm (mucus)
- a persistent or chronic cough such as occurs with smoking, asthma, chronic bronchitis or emphysema

Stop use and ask a doctor if

- cough persists for more than 7 days, tends to recur, or is accompanied by fever, rash, or persistent headache. These could be signs of a serious condition.

If pregnant or breast-feeding,

ask a health professional before use.

Keep out of reach of children.

In case of overdose, get medical help or contact a Poison Control Center right away.

Directions

- do not take more than 6 softgels in a 24 hour period

Age | Dose
adults and children 12 years and older | 1 softgel, every 4 hours
children under 12 years | do not use

Other information

- store between 68-77°F (20-25°C)
- do not use if blister pack is torn or punctured

Inactive ingredients

gelatin, glycerin, polyethylene glycol 400, propylene glycol, povidone k30, sodium hydroxide, sorbitol sorbitan solution, titanium dioxide, water

Questions or comments?

+1-866-359-3478(M-F) 9 AM - 5 PM EST or www.pharmadel.com

Dist. by/ por:

PHARMADEL LLC

New Castle, DE, 19720

+1-866-359-3478